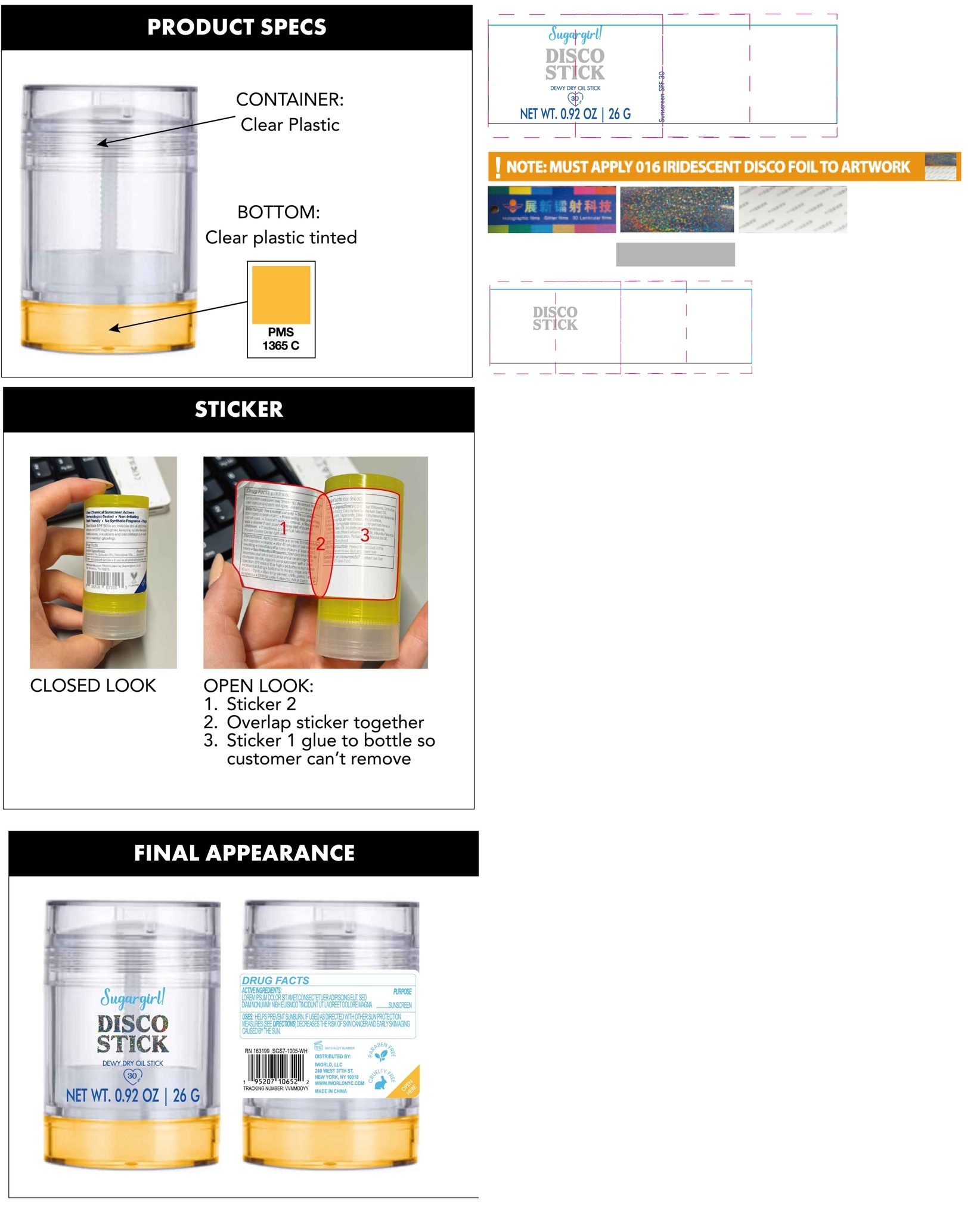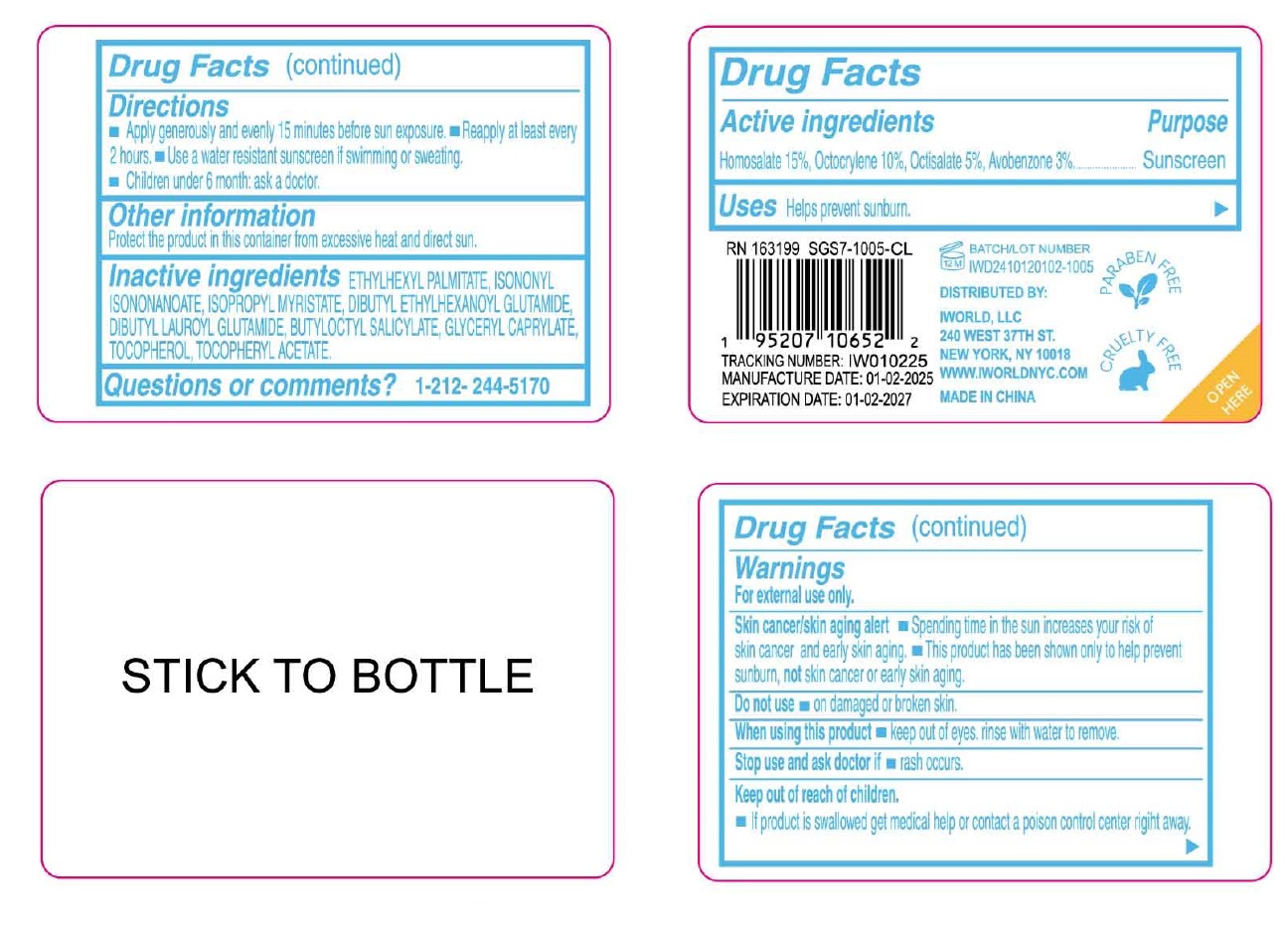 DRUG LABEL: Sugargirl Disco Stick SPF 30
NDC: 85179-001 | Form: STICK
Manufacturer: I World LLC
Category: otc | Type: HUMAN OTC DRUG LABEL
Date: 20250120

ACTIVE INGREDIENTS: HOMOSALATE 150 mg/1 g; OCTOCRYLENE 100 mg/1 g; OCTISALATE 50 mg/1 g; AVOBENZONE 30 mg/1 g
INACTIVE INGREDIENTS: ETHYLHEXYL PALMITATE; ISONONYL ISONONANOATE; ISOPROPYL MYRISTATE; DIBUTYL ETHYLHEXANOYL GLUTAMIDE; DIBUTYL LAUROYL GLUTAMIDE; BUTYLOCTYL SALICYLATE; GLYCERYL MONOCAPRYLATE; TOCOPHEROL; .ALPHA.-TOCOPHEROL ACETATE

Sugargirl Disco Stick SPF 30

Active ingredients

Homosalate 15%, Octocrylene 10%, Octisalate 5%, Avobenzone 3%

Purpose

Sunscreen

Uses

Helps prevent sunburn.

Warnings

For external use only.

Skin cancer/skin aging alert • Spending time in the sun increases your risk of skin cancer and early skin aging.

• This product has been shown only to help prevent sunburn, not skin cancer or early skin aging.

Do not use

- on damaged or broken skin.

When using this product

- Keep out of eyes. rinse with water to remove.

Stop use and ask doctor if

- rash occurs.

Keep out of reach of children.

- If product is swallowed, get medical help or contact a Poison Control Center right away.

Directions

- Apply generously and evenly 15 minutes before sun exposure.
- Reapply at least every 2 hours.
- Use a water resistant sunscreen if swimming or sweating.
- Children under 6 month: ask a doctor.

Other information

Protect the product in this container from excessive heat and direct sun.

Inactive ingredients

ETHYLHEXYL PALMITATE, ISONONYL ISONONANOATE, ISOPROPYL MYRISTATE, DIBUTYL ETHYLHEXANOYL GLUTAMIDE, DIBUTYL LAUROYL GLUTAMIDE, BUTYLOCTYL SALICYLATE, GLYCERYL CAPRYLATE, TOCOPHEROL, TOCOPHERYL ACETATE.

Questions or comments?

1-212-244-5170